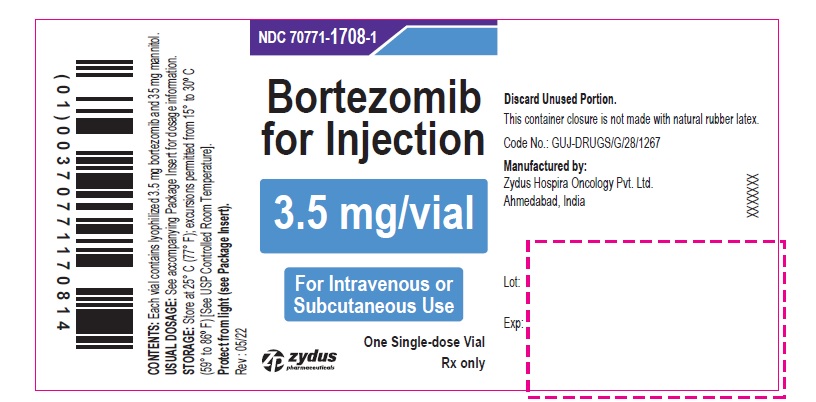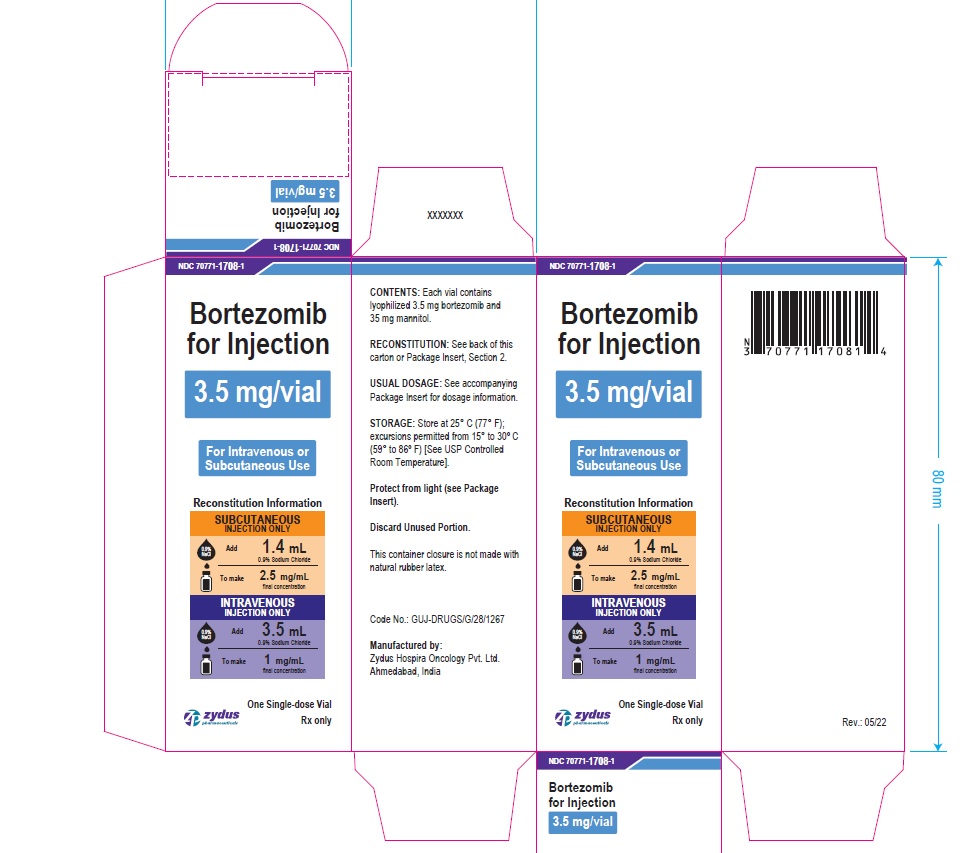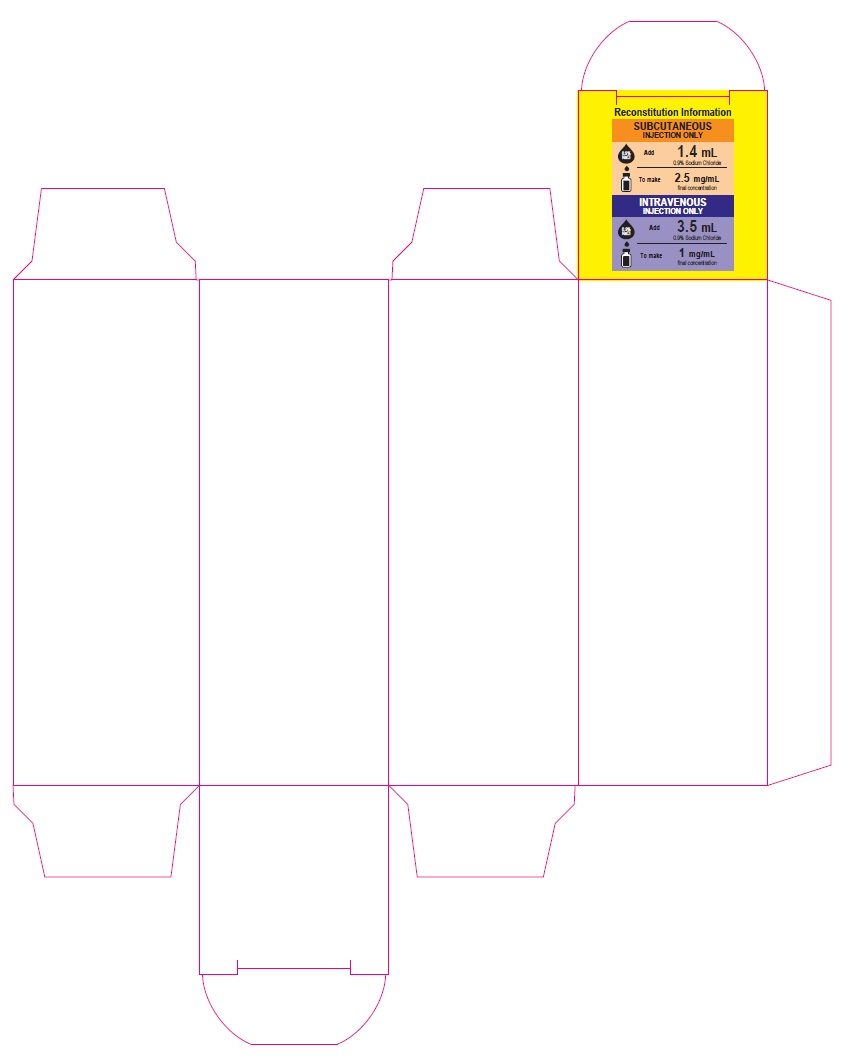 DRUG LABEL: BORTEZOMIB
NDC: 70771-1708 | Form: INJECTION, POWDER, LYOPHILIZED, FOR SOLUTION
Manufacturer: Zydus Lifesciences Limited
Category: prescription | Type: HUMAN PRESCRIPTION DRUG LABEL
Date: 20220505

ACTIVE INGREDIENTS: BORTEZOMIB 1 mg/1 mL
INACTIVE INGREDIENTS: MANNITOL

BORTEZOMIB for injection, for subcutaneous or intravenous use

PACKAGE LABEL.PRINCIPAL DISPLAY PANEL

NDC 70771-1708-1

Bortezomib for Injection

3.5 mg/vial

For Intravenous or Subcutaneous Use

One Single-dose Vial

Rx only

NDC 70771-1708-1

Bortezomib for Injection – Carton label

3.5 mg/vial

For Intravenous or Subcutaneous Use

Reconstitution Information

SUBCUTANEOUS INJECTION ONLY

0.9% NaCl

Add

1.4 mL

0.9% Sodium Chloride

To make

2.5 mg/mL

final concentration

INTRAVENOUS INJECTION ONLY

0.9% NaCl

Add

3.5 mL

0.9% Sodium Chloride

To make

1 mg/mL

final concentration

One Single-dose Vial

Rx only

Reconstitution Information – Inside Flap (All cartons)

SUBCUTANEOUS INJECTION ONLY

0.9% NaCl

Add

1.4 mL

0.9% Sodium Chloride

To make

2.5 mg/mL

final concentration

INTRAVENOUS INJECTION ONLY

0.9% NaCl

Add

3.5 mL

0.9% Sodium Chloride

To make

1 mg/mL

final concentration